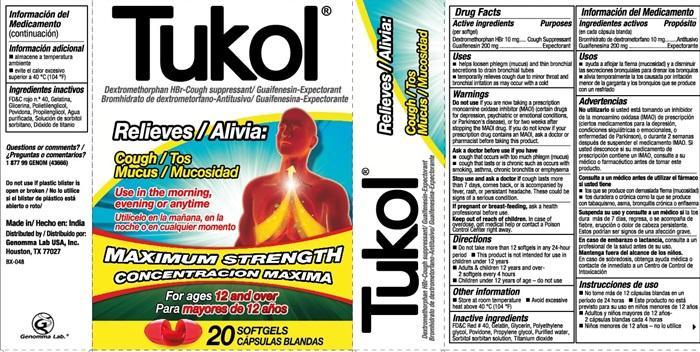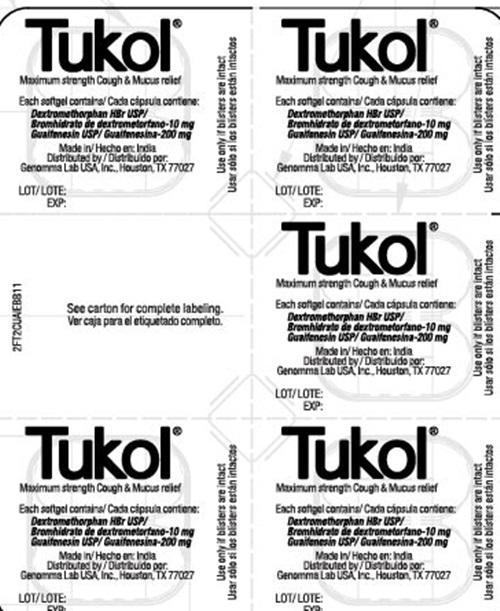 DRUG LABEL: Tukol Maxium Strength Cough and Mucus Relief
NDC: 50066-601 | Form: CAPSULE, GELATIN COATED
Manufacturer: Genomma Lab USA, Inc
Category: otc | Type: HUMAN OTC DRUG LABEL
Date: 20150311

ACTIVE INGREDIENTS: DEXTROMETHORPHAN HYDROBROMIDE 10 mg/1 1; GUAIFENESIN 200 mg/1 1
INACTIVE INGREDIENTS: FD&C RED NO. 40; GELATIN; GLYCERIN; POLYETHYLENE GLYCOLS; POVIDONES; PROPYLENE GLYCOL; WATER; SORBITOL; SORBITAN; TITANIUM DIOXIDE

Drug Facts Active ingredients

Dextromethorphan HBr 10 mg
Guaifenesin 200 mg

Purpose

Cough Suppressant
Expectorant

Keep out of reach of children

In case of overdose, get medical help or contact a Poison Control Center right away.

Uses

- helps loosen phlegm (mucus) and thin bronchial secretions to drain bronchial tubes
- temporarily relieves cough due to minor throat and bronchial irritation as may occur with a cold

Warnings Do not use

if you are now taking a prescription monoamine oxidase inhibitor (MAOI) (certain drugs for depression, psychiatric, or emotional conditions, or Parkinson's disease), or for 2 weeks after stopping the MAOI drug. If you do not know if your prescription drug contains an MAOI, ask a doctor or pharmacist before taking this product.

Ask a doctor before use if you have

- cough that occurs with too much phlegm (mucus)
- cough that lasts or is chronic such as occurs with smoking, asthma, chronic bronchitis or emphysema

Stop use and ask a doctor if

cough lasts more than 7 days, comes back, or is accompanied by fever, rash, or persistent headache. These could be signs of a serious condition.

If pregnant or breast-feeding

ask a health professional before use.

Directions

- Do not take more than 12 softgels in any 24-hour period
- This product is not intended for use in children under 12 years
- Adults and children 12 years and over - 2 softgels every 4 hours
- Children under 12 years of age - do not use

Other information

- Store at room temperature
- Avoid excessive heat above 40° C (104° F)

Inactive ingredients

FD and C Red # 40, Gelatin, Glycerin, Polyethylene glycol, Povidone, Propylene glycol, Purified water, Sorbitol sorbitan solution, Titanium dioxide

Questions or comments?

1-877-99 GENOM (43666)

Tukol Maximum Strength Cough and Mucus Relief Label

Tukol®

Dextromethorphan HBr-Cough suppressant / Guaifensin-Expectorant

Relieves

Cough
Mucus

Use in the morning, evening or anytime

MAIMUM STRENGTH

For ages 12 and over

20 SOFTGELS

Do not use if plastic blister is open or broken

Made in India
Distributed by Genomma Lab USA, Inc. Houston, TX 77027

BX - 048